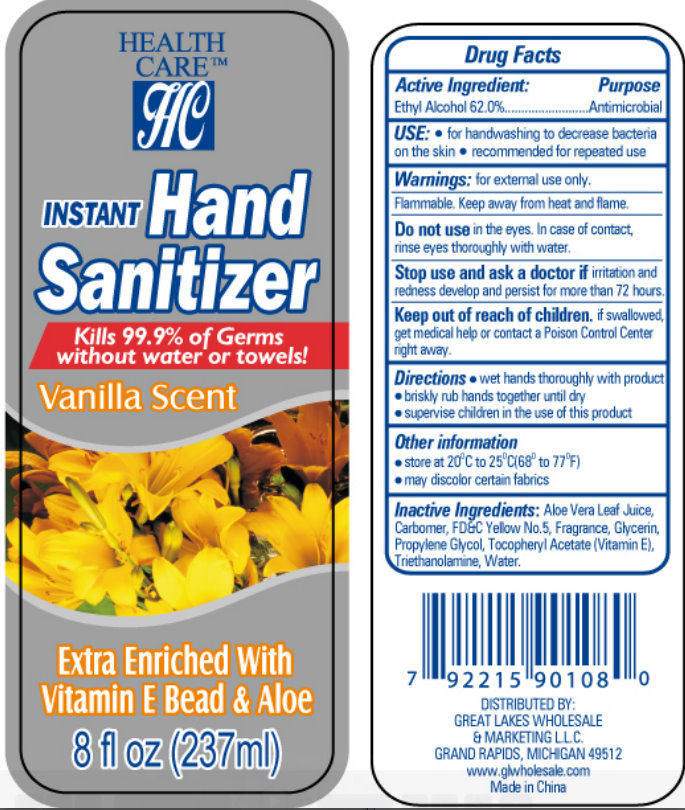 DRUG LABEL: HEALTHCARE Instant Hand Sanitizer Vanilla Scent
NDC: 64092-108 | Form: LIQUID
Manufacturer: GREAT LAKES WHOLESALE, MARKETING, & SALES, INC.
Category: otc | Type: HUMAN OTC DRUG LABEL
Date: 20110810

ACTIVE INGREDIENTS: ALCOHOL 62 mL/100 mL
INACTIVE INGREDIENTS: ALOE VERA LEAF; FD&C YELLOW NO. 5; GLYCERIN; PROPYLENE GLYCOL; ALPHA-TOCOPHEROL; TROLAMINE; WATER

HEALTHCARE Instant Hand Sanitizer Vanilla Scent Extra Enriched With Vitamin E Bead & Aloe

Drug Facts

Active Ingredient:

Ethyl Alcohol 62.0%

Purpose

Antimicrobial

USE:

- for handwashing to decrease bacteria on the skin
- recommended for repeated use

Warnings: for external use only.

STORAGE AND HANDLING

Flammable. Keep away from heat and flame.

Do not use in the eyes. In case of contact, rinse eyes thoroughly with water.

Stop use and ask a doctor if irritation and redness develop and persist for more than 72 hours.

Keep out of reach of children. If swallowed, get medical help or contact a Poison Control Center right away.

Directions

- wet hands thoroughly with product
- briskly rub hands together until dry
- supervise children in the use of this product

Other information

- store at 20 degrees C to 25 degrees C (68 degrees to 77 degrees F)
- may discolor certain fabrics

Inactive Ingredients:

Aloe Vera Leaf Juice, Carbomer, FD C Red No.33, Fragrance, Glycerin, Propylene Glycol, Tocopheryl Acetate (Vitamin E), Triethanolamine, Water.

DISTRIBUTED BY:

GREAT LAKES WHOLESALE

AND MARKETING L.L.C

GRAND RAPIDS, MICHIGAN 49512

www.glwholesale.com

Made in China

PACKAGE LABEL

HEALTH

CARE

INSTANT HAND SANITIZER

Kills 99.9% of Germs without water or towels!

Vanilla Scent

Extra Enriched With Vitamin E Bead And Aloe

8 fl oz (237 ml)